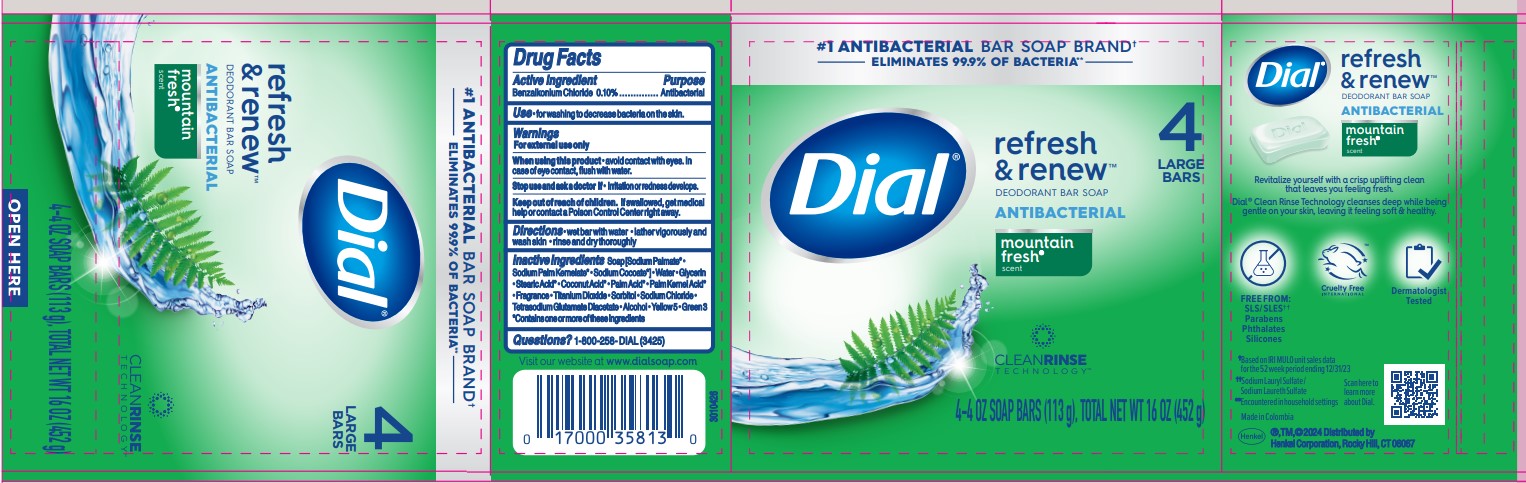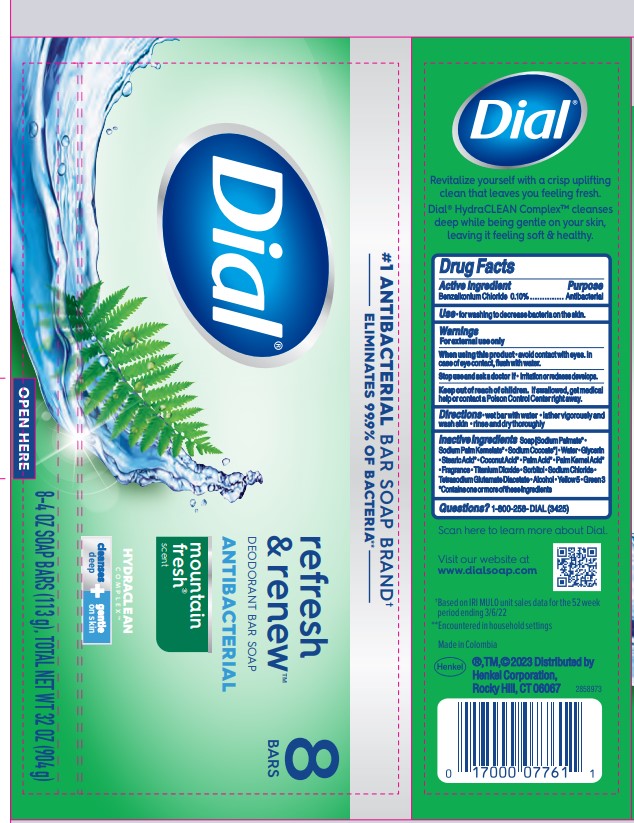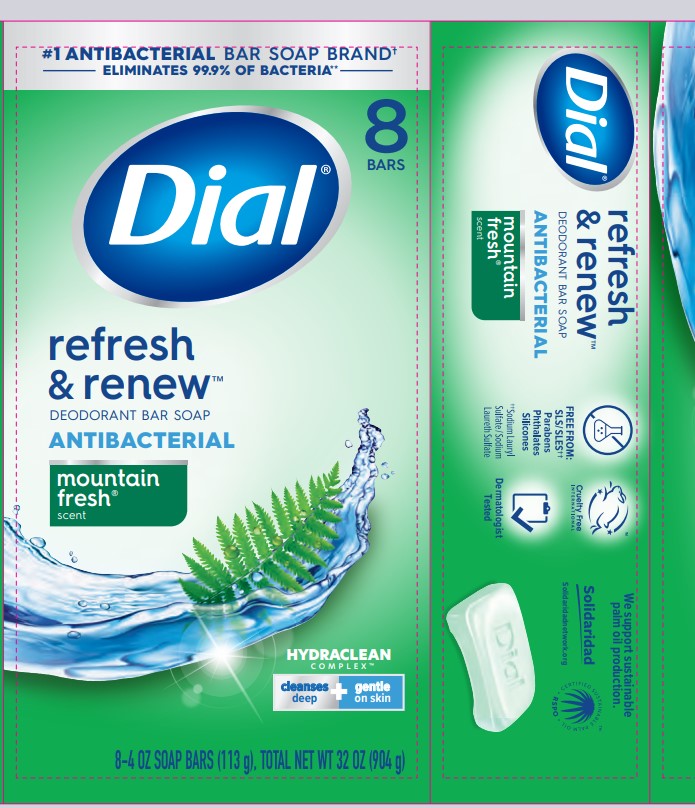 DRUG LABEL: Dial Antibacterial Bar
NDC: 54340-274 | Form: SOAP
Manufacturer: Henkel Corporation
Category: otc | Type: HUMAN OTC DRUG LABEL
Date: 20251114

ACTIVE INGREDIENTS: BENZALKONIUM CHLORIDE 0.1 g/100 g
INACTIVE INGREDIENTS: GLYCERIN; WATER 13.88 g/100 g; ALCOHOL 0.01 g/100 g; SODIUM PALM KERNELATE; TETRASODIUM GLUTAMATE DIACETATE 0.058 g/100 g; FD&C GREEN NO. 3 0.001 g/100 g; BASIC YELLOW 57 0.0063 g/100 g; STEARIC ACID 2.42 g/100 g; SODIUM PALMATE 61.85 g/100 g; TITANIUM DIOXIDE 0.5 g/100 g; SORBITOL; SODIUM CHLORIDE 0.388 g/100 g

Dial Mountain Fresh
Dial Mountain Fresh Antibacterial Soap
Dial Mountain Fresh Antibacterial Deodarant Bar
Dial Refresh& Renew Deodorant Bar Soap Antibacterial Mountain Fresh Scent

Active Ingredient

Benzalkonium Chloride 0.1%

Purpose

Antibacterial

Uses

For washing to decrease the bacteria on the skin.

Warning

For external use only.

When using this product avoid contact with eyes. In case of eye contact, flush with water.

Stop using and ask doctor if irritation or redness develops.

Keep out of reach of children

If swallowed, get medical help or contact Poison Control Center right away.

Directions

wet bar with water

lather vigorously and wash skin

rinse and dry thoroughly

Inactive Ingredient

Sodium Palmate
Water
Sodium Palm Kernelate

Sodium Palmate

Sodium Cocoate
Glycerin
Stearic Acid

Palm Acid

Palm Kernel Acid

Coconut Acid
Fragrance
CI 77891 (Titanium Dioxide)
Sodium Chloride
Sorbitol
Tetrasodium Glutamate Diacetate
Alcohol
CI 19140 (Yellow 5)
CI 42053 (Green 3)

CONTAINS ONE OR MORE OF THESE INGREDIENTS